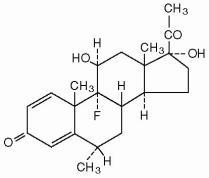 DRUG LABEL: Unknown
Manufacturer: Novartis Ophthalmics
Category: prescription | Type: HUMAN PRESCRIPTION DRUG LABELING
Date: 20060511

Fluor-Op®

Fluor-Op®

(FLUOROMETHOLONE OPHTHALMIC SUSPENSION, USP) 0.1%

DESCRIPTION

FLUOR-OP (fluorometholone ophthalmic suspension, USP) 0.1%, is a topical anti-inflammatory agent for ophthalmic use.

Chemical Name: 9-fluoro-11ß,17-dihydroxy-6α-methylpregna-1,4-diene-3,20-dione.

Contains:

Fluorometholone 0.1%

with: polyvinyl alcohol 1.4%; benzalkonium chloride 0.004%, edetate disodium; sodium chloride; sodium phosphate monobasic, monohydrate; sodium phosphate dibasic, anhydrous; polysorbate 80; sodium hydroxide to adjust the pH, and purified water.

CLINICAL PHARMACOLOGY

Corticosteroids inhibit the inflammatory response to a variety of inciting agents and probably delay or slow healing. They inhibit the edema, fibrin deposition, capillary dilation, leukocyte migration, capillary proliferation, fibroblast proliferation, deposition of collagen, and scar formation associated with inflammation.

There is no generally accepted explanation for the mechanism of action of ocular corticosteroids. However, corticosteroids are thought to act by the induction of phospholipase A2 inhibitory proteins, collectively called lipocortins. It is postulated that these proteins control the biosynthesis of potent mediators of inflammation such as prostaglandins and leukotrienes by inhibiting the release of their common precursor, arachidonic acid. Arachidonic acid is released from membrane phospholipids by phospholipase A2.

Corticosteroids are capable of producing a rise in intraocular pressure. In clinical studies on patients' eyes treated with both dexamethasone and fluorometholone 0.1% suspensions, fluorometholone demonstrated a lower propensity to increase intraocular pressure than did dexamethasone.

INDICATIONS AND USAGE

FLUOR-OP is indicated for the treatment of corticosteroid-responsive inflammation of the palpebral and bulbar conjunctiva, cornea and anterior segment of the globe.

CONTRAINDICATIONS

FLUOR-OP suspension is contraindicated in most viral diseases of the cornea and conjunctiva, including epithelial herpes simplex keratitis (dendritic keratitis), vaccinia, and varicella, and also in mycobacterial infection of the eye and fungal diseases of ocular structures. FLUOR-OP suspension is also contraindicated in individuals with known or suspected hypersensitivity to any of the ingredients of this preparation and to other corticosteroids.

WARNINGS

Prolonged use of corticosteroids may result in glaucoma with damage to the optic nerve, defects in visual acuity and fields of vision, and in posterior subcapsular cataract formation. Prolonged use may suppress the host immune response and thus increase the hazard of secondary ocular infections.

Various ocular diseases and long-term use of topical corticosteroids have been known to cause corneal and scleral thinning. Use of topical corticosteroids in the presence of thin corneal or scleral tissue may lead to perforation.

Acute purulent untreated infections of the eye may be masked or activity enhanced by the presence of corticosteroid medication.

If this product is used for 10 days or longer, intraocular pressure should be routinely monitored even though it may be difficult in children and uncooperative patients. Steroids should be used with caution in the presence of glaucoma. Intraocular pressure should be checked frequently.

The use of steroids after cataract surgery may delay healing and increase the incidence of bleb formation.

Use of ocular steroids may prolong the course and may exacerbate the severity of many viral infections of the eye (including herpes simplex). Employment of a corticosteroid medication in the treatment of patients with a history of herpes simplex requires great caution; frequent slit lamp microscopy is recommended.

Corticosteroids are not effective in mustard gas keratitis and Sjögren’s keratoconjunctivitis.

PRECAUTIONS

General

The initial prescription and renewal of the medication order beyond 20 milliliters of FLUOR-OP suspension should be made by a physician only after examination of the patient with the aid of magnification, such as slit lamp biomicroscopy and, where appropriate, fluorescein staining. If signs and symptoms fail to improve after two days, the patient should be re-evaluated.

As fungal infections of the cornea are particularly prone to develop coincidentally with long-term local corticosteroid applications, fungal invasion should be suspected in any persistent corneal ulceration where a corticosteroid has been used or is in use. Fungal cultures should be taken when appropriate.

If this product is used for 10 days or longer, intraocular pressure should be monitored (see WARNINGS).

Information to the Patient

If inflammation or pain persists longer than 48 hours or becomes aggravated, the patient should be advised to discontinue use of the medication and consult a physician.

This product is sterile when packaged. To prevent contamination, care should be taken to avoid touching the bottle tip to eyelids or to any other surface. The use of this bottle by more than one person may spread infection. Keep bottle tightly closed when not in use. Keep out of reach of children.

Carcinogenesis, mutagenesis, impairment of fertility

No studies have been conducted in animals or in humans to evaluate the possibility of these effects with fluorometholone.

Pregnancy

Teratogenic effects. Pregnancy Category C

Fluorometholone has been shown to be embryocidal and teratogenic in rabbits when administered at low multiples of the human ocular dose. Fluorometholone was applied ocularly to rabbits daily on days 6-18 of gestation, and dose related fetal loss and fetal abnormalities including cleft palate, deformed rib cage, anomalous limbs and neural abnormalities such as encephalocele, craniorachischisis, and spina bifida were observed. There are no adequate and well-controlled studies of fluorometholone in pregnant women, and it is not known whether fluorometholone can cause fetal harm when administered to a pregnant women. Fluorometholone should be used during pregnancy only if the potential benefit justifies the potential risk to the fetus.

Nursing Mothers

It is not known whether topical ophthalmic administration of corticosteroids could result in sufficient systemic absorption to produce detectable quantities in human milk. Systemically administered corticosteroids appear in human milk and could suppress growth, interfere with endogenous corticosteroid production, or cause other untoward effects. Because of the potential for serious adverse reactions in nursing infants from fluorometholone, a decision should be made whether to discontinue nursing or to discontinue the drug, taking into account the importance of the drug to the mother.

Pediatric Use

Safety and effectiveness in children below the age of two years have not been established.

ADVERSE REACTIONS

Adverse reactions include, in decreasing order of frequency, elevation of intraocular pressure (IOP) with possible development of glaucoma and infrequent optic nerve damage, posterior subcapsular cataract formation, and delayed wound healing.

Although systemic effects are extremely uncommon, there have been rare occurrences of systemic hypercorticoidism after use of topical steroids.

Corticosteroid-containing preparations have also been reported to cause acute uveitis and perforation of the globe. Keratitis, conjunctivitis, corneal ulcers, mydriasis, conjunctival hyperemia, loss of accommodation and ptosis have occasionally been reported following use of corticosteroids.

The development of secondary ocular infection (bacterial, fungal and viral) has occurred. Fungal and viral infections of the cornea are particularly prone to develop coincidentally with long-term applications of steroids. The possibility of fungal invasion should be considered in any persistent corneal ulceration where steroid treatment has been used (see WARNINGS).

DOSAGE AND ADMINISTRATION

Instill one drop into the conjunctival sac two to four times daily. During the initial 24 to 48 hours, the dosage may be increased to one application every four hours. Care should be taken not to discontinue therapy prematurely.

If signs and symptoms fail to improve after two days, the patient should be re-evaluated (see PRECAUTIONS).

The dosing of FLUOR-OP suspension may be reduced, but care should be taken not to discontinue therapy prematurely. In chronic conditions, withdrawal of treatment should be carried out by gradually decreasing the frequency of applications.

HOW SUPPLIED

FLUOR-OP (fluorometholone ophthalmic suspension, USP) 0.1% is supplied in plastic dropper bottles in the following sizes:

5 mL…………………………………………………………………………..NDC 58768-358-05

10 mL…………………………………………………………………………NDC 58768-358-10

15 mL…………………………………………………………………………NDC 58768-358-15

Store at controlled room temperature 15°-30°C (59°-86°F). Protect from freezing. Shake well before using. Keep bottle tightly closed when not in use.

Rx only

Mfd. by OMJ Pharmaceuticals, Inc.,

San Germán, P.R., 00683 for:

Novartis Ophthalmics

Duluth, GA 30097

6069-B